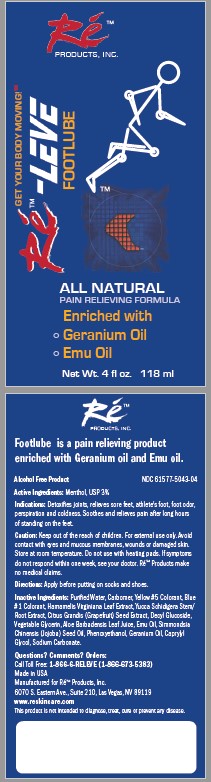 DRUG LABEL: RE-LEVE FOOTLUBE PAIN RELIEF
NDC: 61577-5042 | Form: GEL
Manufacturer: SOMBRA COSMETICS INC.
Category: otc | Type: HUMAN OTC DRUG LABEL
Date: 20221128

ACTIVE INGREDIENTS: MENTHOL 0.03 g/1 g
INACTIVE INGREDIENTS: WATER; CARBOMER COPOLYMER TYPE A; FD&C BLUE NO. 1; FD&C YELLOW NO. 5; WITCH HAZEL; YUCCA SCHIDIGERA STEM; GRAPEFRUIT SEED OIL; DECYL GLUCOSIDE; GLYCERIN; ALOE VERA LEAF; EMU OIL; JOJOBA OIL; PHENOXYETHANOL; GERANIUM OIL, ALGERIAN TYPE; CAPRYLYL GLYCOL

Re-LEVE Footlube Pain Relief

Active Ingredients

Menthol USP 3%

Purpose

External Analgesic

Keep out of the reach of children

Uses

Detoxifies joints, relieves sore feet, athletes foot, foot odor, perspiration and coldness. Soothes and relieves pain after long hours of standing on feet.

Warnings

Keep out of the reach of children. For external use only. Aviod contact with eyes and mucous membranes, wounds or damaged skin. Store at room temperature. Do not use with heating pads. If symtoms do not respond within one week, see doctor. ReLEVE Products makes no medical claims.

Directions

Apply before putting on socks and shoes.

Inactive Ingredients

Purified water, Carbomer, Yellow #5 Colorant, Blue #1 Colorant, Hamamelis Viriniana Leaf Extract, Yucca Schidigera Stem/Root Extract, Citrus Grandis (Grapefruit) Seed Extract, Decyl Glucoside, Vegetable Glycerin, Aloe Barbadensis Leaf Juice, Emu Oil, Simmondsia Chinensis (Jojoba) Seed oil, Phenoxyethanol, Germanium oil, Caprylyl Glycol, Sodium Carbonate.

Questions or Comments?

Call Toll Free: 1-866-673-5383, 6070 S. Eastern Ave. Suite 210, Las Vegas, NV 89119, www.reskincare.com